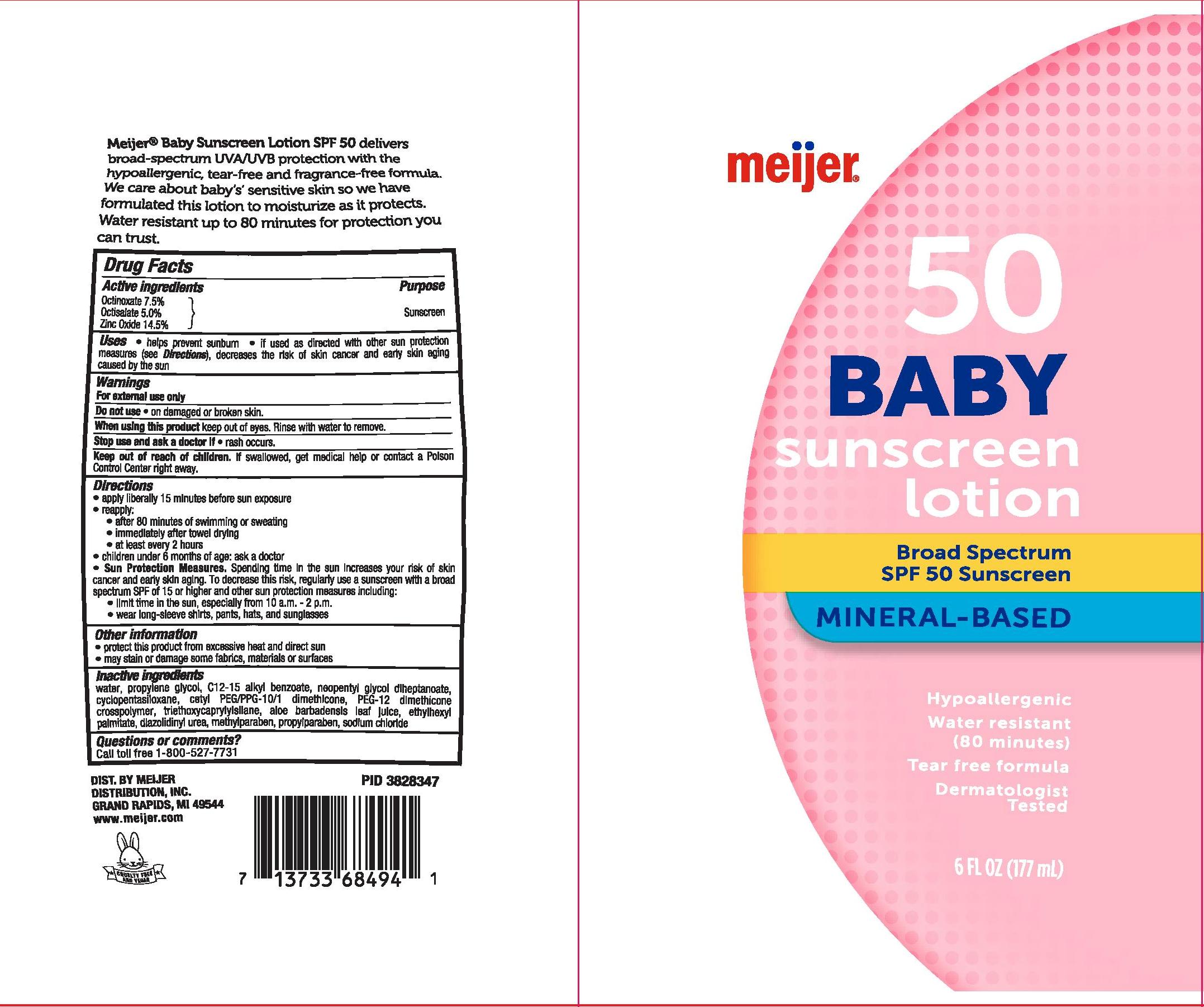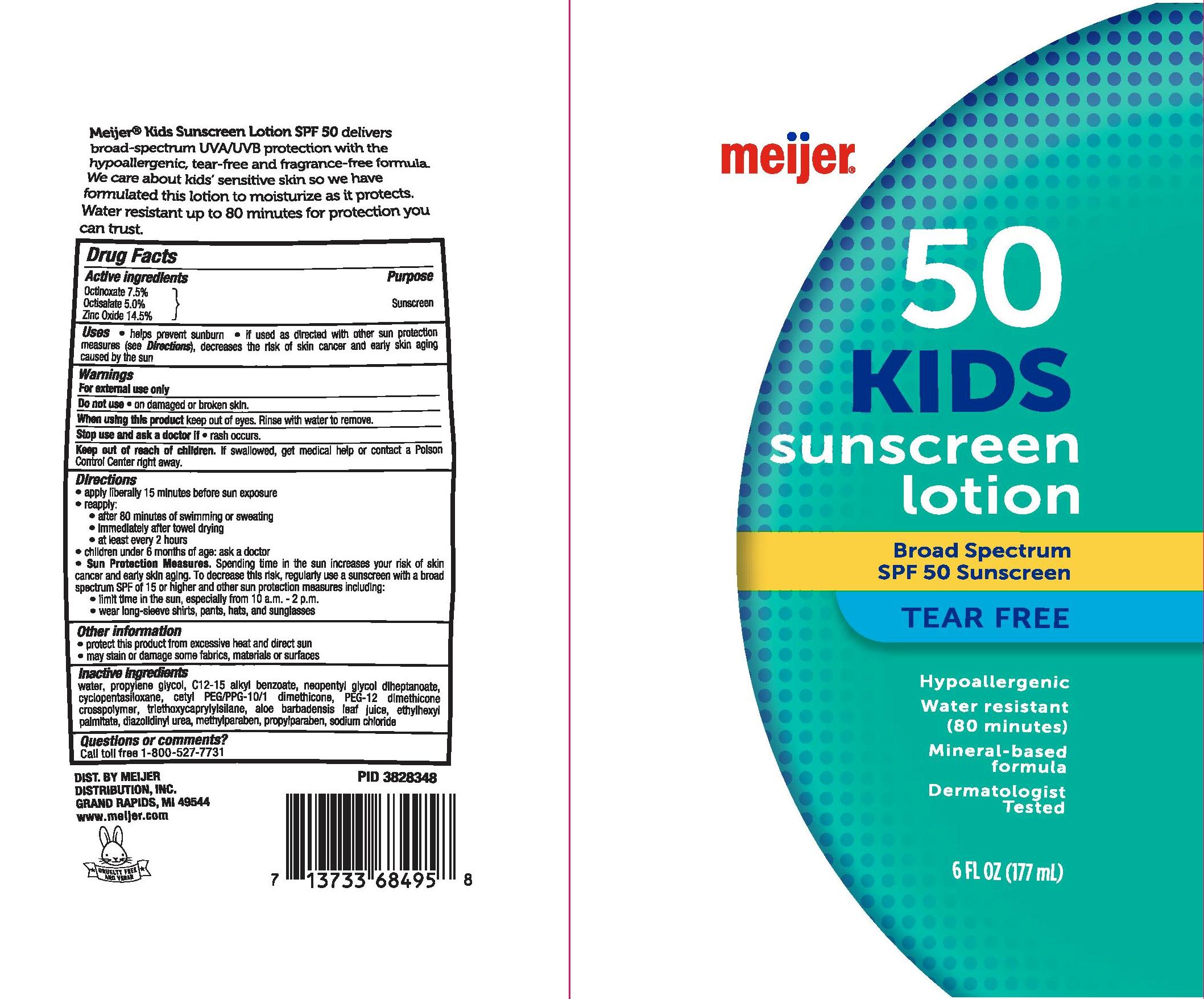 DRUG LABEL: MEIJER KIDS BROAD SPECTRUM SPF 50 MINERAL BASED SUNSCREEN
NDC: 41250-362 | Form: LOTION
Manufacturer: MEIJER DISTRIBUTION INC
Category: otc | Type: HUMAN OTC DRUG LABEL
Date: 20241016

ACTIVE INGREDIENTS: ZINC OXIDE 145 mg/1 mL; OCTISALATE 50 mg/1 mL; OCTINOXATE 75 mg/1 mL
INACTIVE INGREDIENTS: WATER; ALKYL (C12-15) BENZOATE; CYCLOMETHICONE 5; CETYL PEG/PPG-10/1 DIMETHICONE (HLB 5); TRIETHOXYCAPRYLYLSILANE; DIAZOLIDINYL UREA; METHYLPARABEN; PROPYLPARABEN; SODIUM CHLORIDE; PROPYLENE GLYCOL; ALOE VERA LEAF; ETHYLHEXYL PALMITATE; NEOPENTYL GLYCOL DIHEPTANOATE

MEIJER KIDS BROAD SPECTRUM SPF 50 MINERAL-BASED SUNSCREEN LOTION

Active ingredients

Octinoxate 7.5%, Octisalate 5.0%, Zinc Oxide 14.5%

Purpose

Sunscreen

Uses

- helps prevent sunburn
- if used as directed with othersun protection measures (see Directions), decreases the risk of skin cancer and early skin aging casued by the sun

Warnings

For external use only

Do not use

- on damaged or broken skin.

When using this product

keep out of eyes. Rinse with water to remove.

Stop use and ask a doctor if

- rash occurs.

Keep out of reach of children.

If swallowed, get medical help or contact a Poison Control Center right away.

Directions

- apply liberally 15 minutes before sun exposure
- reapply:
- after 80 minutes of swimming or sweating
- immediately after towel drying
- at least every 2 hours
- children under 6 months of age: Ask a doctor
- Sun Protection Measures. Spending time in the sun increases your risk of skin cancer and early skin aging. To decrease this risk, regularly use a sunscreen with a Broad Spectrum SPF value of 15 or higher and other sun protection measures including:
- limit time in the sun, especially from 10 a.m.-2 p.m.
- wear long-sleeved shirts, pants, hats, and sunglasses

Other information

- protect the product in this container from excessive heat and direct sun
- may stain or damage some fabrics, materials or surfaces

Inactive ingredients

water, propylene glycol, C12-15 alkyl benzoate, neopentyl glycol diheptanoate, cyclopentasiloxane, cetyl PEG/PPG-10/1 dimethicone, OEG-12 dimethicone crosspolymer, triethoxycaprylylsilane, aloe barbadensis leaf juice, ethylhexyl palmitate, diazolidinyl urea, methylparaben, propylparaben, sodium chloride